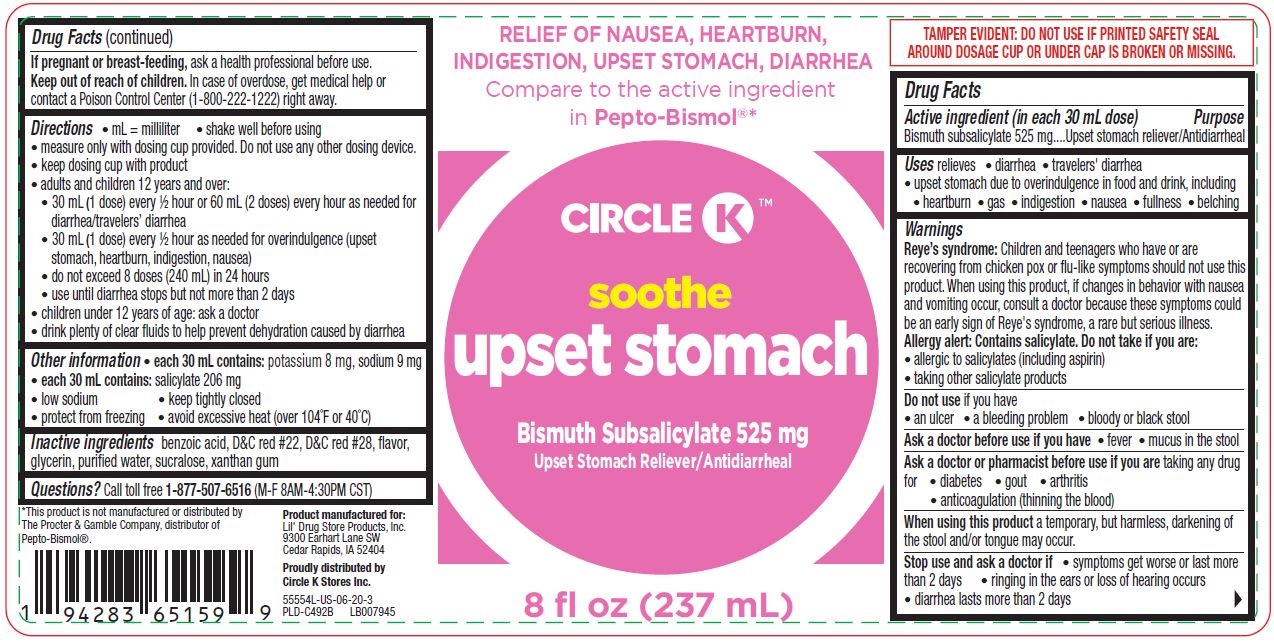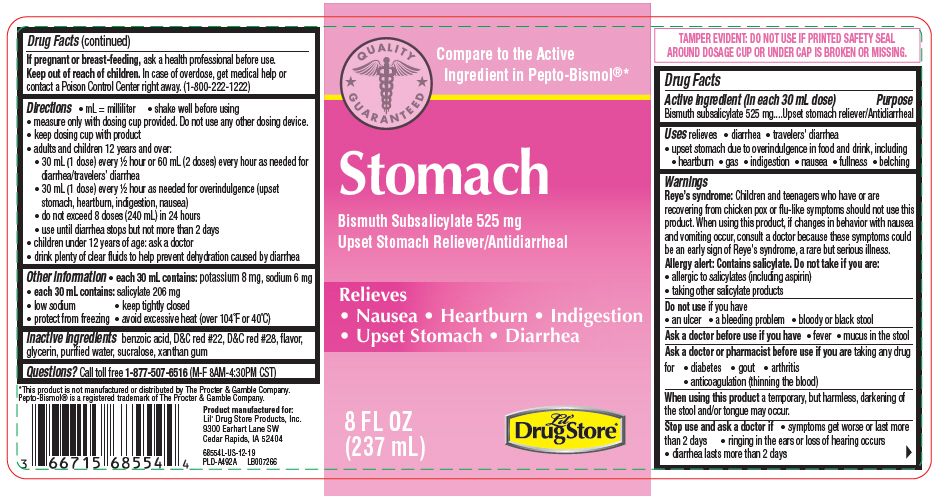 DRUG LABEL: Stomach
NDC: 66715-6855 | Form: LIQUID
Manufacturer: Lil' Drug Store Products, Inc
Category: otc | Type: HUMAN OTC DRUG LABEL
Date: 20240506

ACTIVE INGREDIENTS: BISMUTH SUBSALICYLATE 525 mg/30 mL
INACTIVE INGREDIENTS: BENZOIC ACID; D&C RED NO. 22; D&C RED NO. 28; GLYCERIN; WATER; SUCRALOSE; XANTHAN GUM

Lil' Drug Store® Stomach

Drug Facts

Active ingredient (in each 30 mL dose)

Bismuth subsalicylate 525 mg

Purpose

Upset stomach reliever/Antidiarrheal

Uses

relieves

- diarrhea
- travelers' diarrhea
- upset stomach due to overindulgence in food and drink, including
  - heartburn
  - gas
  - indigestion
  - nausea
  - fullness
  - belching

Warnings

Reye's syndrome

Children and teenagers who have or are recovering from chicken pox or flu-like symptoms should not use this product. When using this product, if changes in behavior with nausea and vomiting occur, consult a doctor because these symptoms could be an early sign of Reye's syndrome, a rare but serious illness.

Allergy alert

Contains salicylate. Do not take if you are:

- allergic to salicylates (including aspirin)
- taking other salicylate products

Do not use if you have

- an ulcer
- a bleeding problem
- bloody or black stool

Ask a doctor before use if you have

- fever
- mucus in the stool

Ask a doctor or pharmacist before use if you are taking any drug for

- diabetes
- gout
- arthritis
- anticoagulation (thinning the blood)

When using this product a temporary, but harmless, darkening of the stool and/or tongue may occur.

Stop use and ask a doctor if

- symptoms get worse or last more than 2 days
- ringing in the ears or loss of hearing occurs
- diarrhea lasts more than 2 days

PREGNANCY OR BREAST FEEDING

If pregnant or breast-feeding, ask a health professional before use.

Keep out of reach of children. In case of overdose, get medical help or contact a Poison Control Center right away. (1-800-222-1222)

Directions

- mL = milliliter
- shake well before using
- measure only with dosing cup provided. Do not use any other dosing device.
- keep dosing cup with product
- adults and children 12 years and over:
  - 30 mL (1 dose) every ½ hour or 60 mL (2 doses) every hour as needed for diarrhea/travelers' diarrhea
  - 30 mL (1 dose) every ½ hour as needed for overindulgence (upset stomach, heartburn, indigestion, nausea)
  - do not exceed 8 doses (240 mL) in 24 hours
  - use until diarrhea stops but not more than 2 days
- children under 12 years of age: ask a doctor
- drink plenty of clear fluids to help prevent dehydration caused by diarrhea

Other information

- each 30 mL contains: potassium 8 mg, sodium 6 mg
- each 30 mL contains: salicylate 206 mg
- low sodium
- keep tightly closed
- protect from freezing
- avoid excessive heat (over 104°F or 40°C)

Inactive ingredients

benzoic acid, D&C red #22, D&C red #28, flavor, glycerin, purified water, sucralose, xanthan gum

Questions?

Call toll free 1-877-507-6516 (M-F 8AM-4:30PM CST)

PRINCIPAL DISPLAY PANEL - 237 mL Bottle Label

QUALITY
GUARANTEED

Compare to the Active
Ingredient in Pepto-Bismol®*

Stomach

Bismuth Subsalicylate 525 mg
Upset Stomach Reliever/Antidiarrheal

Relieves
• Nausea • Heartburn • Indigestion
• Upset Stomach • Diarrhea

8 FL OZ
(237 mL)

Lil'
Drug Store®

Circle K™ Soothe Upset Stomach -PDP/Package

RELIEF OF NAUSEA, HEARTBURN,
INDIGESTION, UPSET STOMACH, DIARRHEA
Compare to the active ingredient
in Pepto-Bismol®*

[Circle K logo]

soothe

upset stomach

Bismuth Subsalicylate 525 mg

Upset Stomach Reliever/Antidiarrheal

8 fl oz (237 mL)